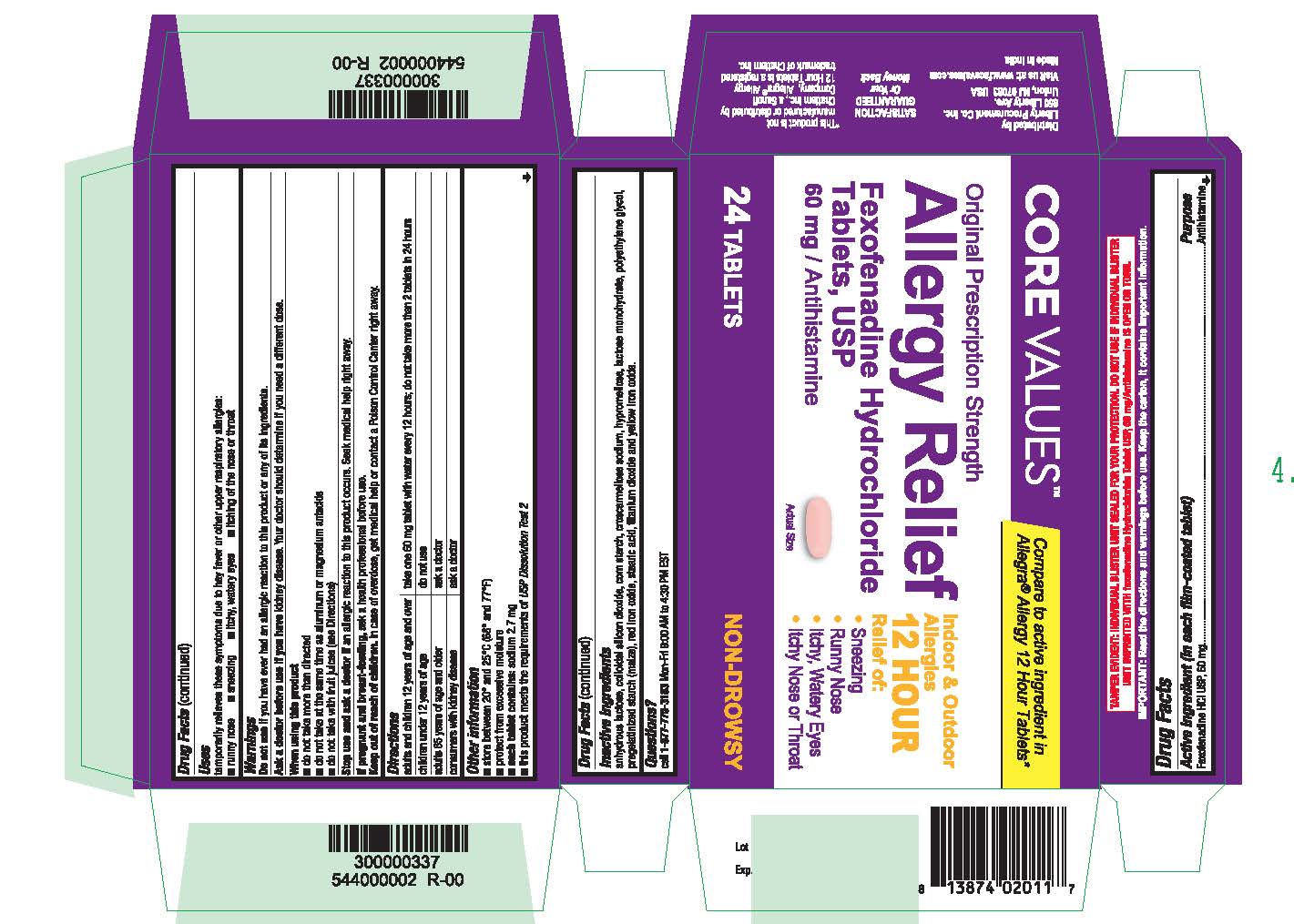 DRUG LABEL: Fexofenadine Hydrochloride
NDC: 63940-768 | Form: TABLET, FILM COATED
Manufacturer: HARMON STORES INC.
Category: otc | Type: HUMAN OTC DRUG LABEL
Date: 20191217

ACTIVE INGREDIENTS: FEXOFENADINE HYDROCHLORIDE 60 mg/1 1
INACTIVE INGREDIENTS: TITANIUM DIOXIDE; CROSCARMELLOSE SODIUM; HYPROMELLOSES; ANHYDROUS LACTOSE; SILICON DIOXIDE; LACTOSE MONOHYDRATE; POLYETHYLENE GLYCOL, UNSPECIFIED; STARCH, PREGELATINIZED CORN; FERRIC OXIDE RED; STEARIC ACID; FERRIC OXIDE YELLOW

Original Prescription Strength
Allergy Relief
Fexofenadine Hydrochloride Tablets, USP
60 mg/Antihistamine
NON-DROWSY
Indoor & Outdoor Allergies

Active ingredient

(in each film-coated tablet)

Fexofenadine HCl USP, 60 mg

Purpose

Antihistamine

Uses

temporarily relieves these symptoms due to hay fever or other upper respiratory allergies:

■ runny nose

■ sneezing

■ itchy, watery eyes

■ itching of the nose or throat

Do not use

if you have ever had an allergic reaction to this product or any of its ingredients.

Ask a doctor before use if you have

kidney disease. Your doctor should determine if you need a different dose.

When using this product

■ do not take more than directed

■ do not take at the same time as aluminum or magnesium antacids

■ do not take with fruit juices (see Directions)

Stop use and ask a doctor if

an allergic reaction to this product occurs. Seek medical help right away.

If pregnant or breast-feeding,

ask a health professional before use.

Keep out of reach of children.

In case of overdose, get medical help or contact a Poison Control Center right away.

Directions

adults and children 12 years of age and over

- take one 60 mg tablet with water every 12 hours; do not take more than 2 tablets in 24 hours

children under 12 years of age

- do not use

adults 65 years of age and older

- ask a doctor

consumers with kidney disease

- ask a doctor

Other Information

■ store between 20° and 25°C (68° and 77°F)

■ protect from excessive moisture

■ each tablet contains: sodium 2.7 mg

■ this product meets the requirements of USP Dissolution Test 2

Inactive ingredients

anhydrous lactose, colloidal silicon dioxide, corn starch, croscarmellose sodium, hypromellose, lactose monohydrate, polyethylene glycol, pregelatinized starch (maize), red iron oxide, stearic acid, titanium dioxide and yellow iron oxide.

Questions?

call 1-877-770-3183 Mon-Fri 9:00 AM to 4:30 PM EST.